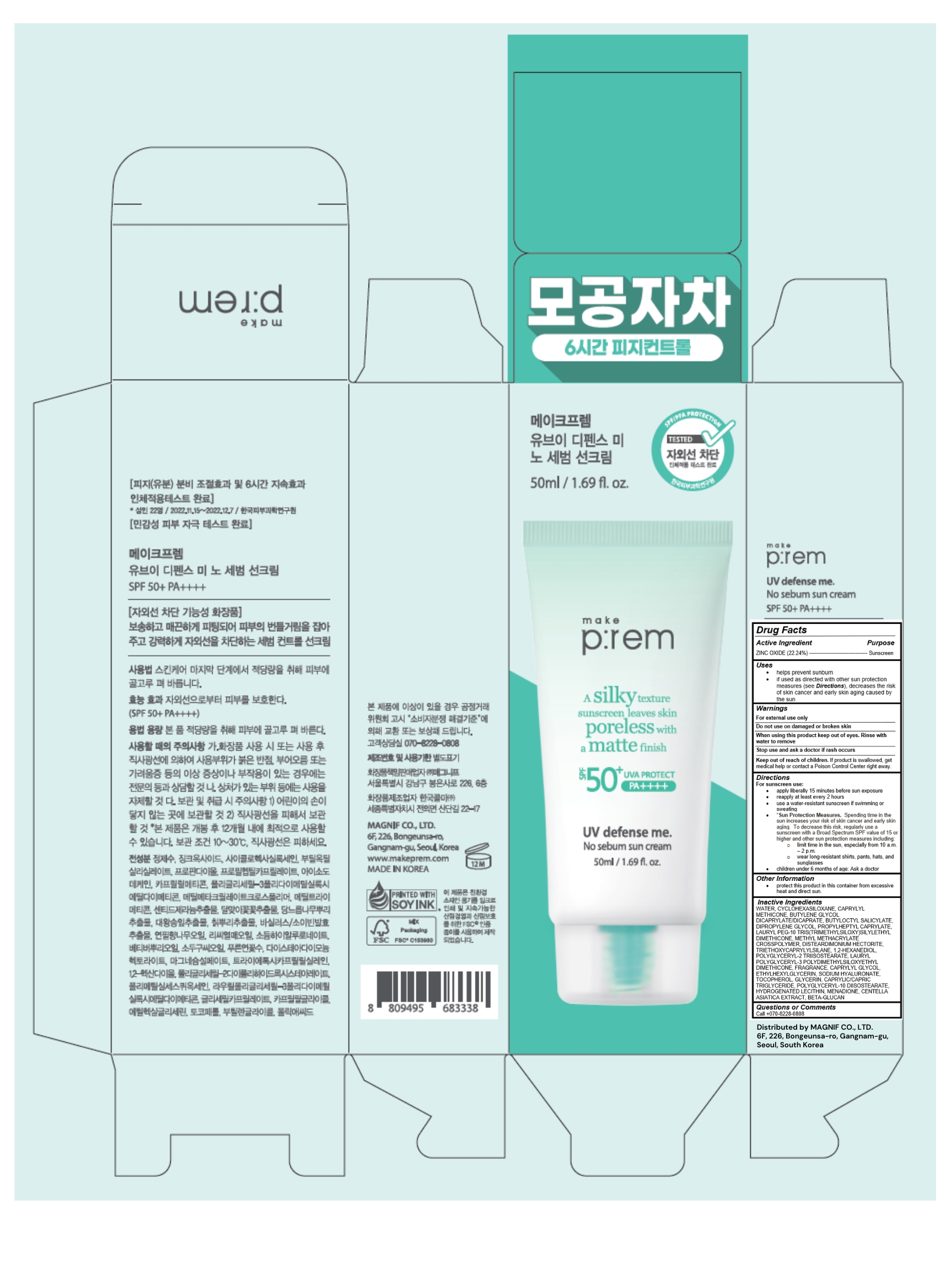 DRUG LABEL: UV defense me. No sebum sunscreen
NDC: 84523-101 | Form: CREAM
Manufacturer: Magnif Co., Ltd
Category: otc | Type: HUMAN OTC DRUG LABEL
Date: 20240718

ACTIVE INGREDIENTS: ZINC OXIDE 11.12 g/50 mL
INACTIVE INGREDIENTS: HYALURONATE SODIUM; GLYCERIN; ETHYLHEXYLGLYCERIN; MENADIONE; BUTYLENE GLYCOL DICAPRYLATE/DICAPRATE; TOCOPHEROL; CAPRYLYL GLYCOL; WATER; DIPROPYLENE GLYCOL; CAPRYLYL TRISILOXANE; BUTYLENE GLYCOL; POLYGLYCERYL-2 TRIISOSTEARATE; CYCLOMETHICONE 6; BUTYLOCTYL SALICYLATE; PROPYLHEPTYL CAPRYLATE; DISTEARDIMONIUM HECTORITE; TRIETHOXYCAPRYLYLSILANE; 1,2-HEXANEDIOL; MEDIUM-CHAIN TRIGLYCERIDES; CENTELLA ASIATICA TRITERPENOIDS

Active Ingredient

ZINC OXIDE (22.24%)

Purpose

Sunscreen

Uses

helps prevent sunburn

if used as directed with other sun protection measures (see Directions), decreases the risk of skin cancer and early skin aging caused by the sun

Keep out of reach of children. If product is swallowed, get medical help or contact a Poison Control Center right away.

Warnings

For external use only

Do not use on damaged or broken skin

When using this product keep out of eyes. Rinse with water to remove.

Stop use and ask a doctor if rash occurs

Keep out of reach of children. If product is swallowed, get medical help or contact a Poison Control Center right away.

Inactive Ingredients

WATER, CYCLOHEXASILOXANE, CAPRYLYL METHICONE, BUTYLENE GLYCOL, DICAPRYLATE/DICAPRATE, BUTYLOCTYL SALICYLATE, DIPROPYLENE GLYCOL, PROPYLHEPTYL CAPRYLATE, LAURYL PEG-10 TRIS(TRIMETHYLSILOXY)SILYLETHYL DIMETHICONE, METHYL METHACRYLATE CROSSPOLYMER, DISTEARDIMONIUM HECTORITE, TRIETHOXYCAPRYLYLSILANE, 1,2-HEXANEDIOL, POLYGLYCERYL-2 TRIISOSTEARATE, LAURYL POLYGLYCERYL-3 POLYDIMETHYLSILOXYETHYL DIMETHICONE, FRAGRANCE, CAPRYLYL GLYCOL, ETHYLHEXYLGLYCERIN, SODIUM HYALURONATE, TOCOPHEROL, GLYCERIN, CAPRYLIC/CAPRIC TRIGLYCERIDE, POLYGLYCERYL-10 DIISOSTEARATE, HYDROGENATED LECITHIN, MENADIONE, CENTELLA ASIATICA EXTRACT, BETA-GLUCAN

Directions

For sunscreen use:

apply liberally 15 minutes before sun exposure
reapply at least every 2 hours
use a water-resistant sunscreen if swimming or sweating
Sun Protection Measures. Spending time in the sun increases your risk of skin cancer and early skin aging. To decrease this risk, regularly use a sunscreen with a Broad Spectrum SPF value of 15 or higher and other sun protection measures including:

limit time in the sun, especially from 10 a.m. – 2 p.m.
wear long-resistant shirts, pants, hats, and sunglasses

children under 6 months of age: Ask a doctor